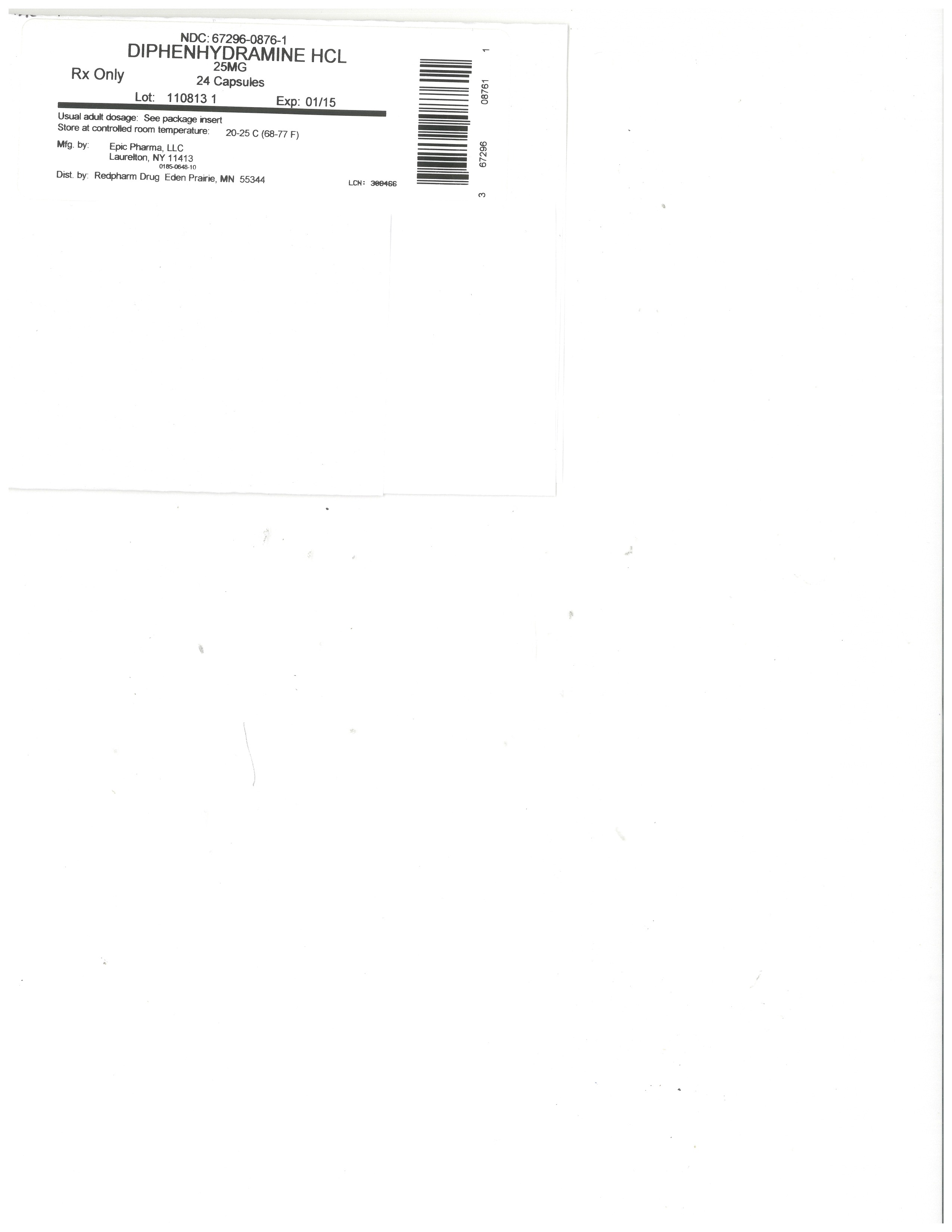 DRUG LABEL: diphenhydramine hydrochloride
NDC: 67296-0876 | Form: CAPSULE
Manufacturer: RedPharm Drug, Inc.
Category: otc | Type: HUMAN OTC DRUG LABEL
Date: 20200120

ACTIVE INGREDIENTS: DIPHENHYDRAMINE HYDROCHLORIDE 25 mg/1 1
INACTIVE INGREDIENTS: SILICON DIOXIDE; STARCH, CORN; ANHYDROUS LACTOSE; MAGNESIUM STEARATE; SODIUM LAURYL SULFATE; FD&C BLUE NO. 1; D&C RED NO. 28; FD&C RED NO. 40; GELATIN

PURPOSE

Antihistamine

USES

Temporarily relieves these symptoms due to hay fever or other upper respiratory allergies

•
runny nose and sneezing
•
itching of the nose or throat
•
itchy, watery eyes.

WARNINGS

Ask a doctor before use if you have

•
a breathing problem such as emphysema or chronic bronchitis
•
glaucoma
•
difficulty in urination due to enlargement of the prostate gland

Do not use with any other product containing diphenhydramine, including products used topically.

Ask a doctor or pharmacist before use if you are

•
taking tranquilizers or sedatives
•
taking other products containing diphenhydramine

When using this product

•
Do not exceed recommended dosage
•
excitability may occur, especially in children
•
marked drowsiness may occur
•
alcohol, sedatives, and tranquilizers may increase drowsiness
•
avoid alcoholic drinks
•
use caution when driving a motor vehicle or operating machinery

If pregnant or breastfeeding ask a health professional before use.

KEEP OUT OF THE REACH OF CHILDREN.

In case of overdose, get medical help or contact a Poison Control Center right away.

DIRECTIONS

•
Adults and Children 12 years and over: 25 to 50 mg (1 to 2 capsules) every 4 to 6 hours, not to exceed 12 capsules in 24 hours.
•
Children 12 years and under: Consult a Doctor

STORAGE AND HANDLING

Keep tightly closed. Store at 20º to 25ºC (68º to 77ºF) [See USP Controlled Room Temperature].

Manufactured for Sandoz Inc.

Princeton, NJ 08540

Manufactured by Epic Pharma, LLC

Laurelton, NY 11413

L1812

Rev. 11/08

INACTIVE INGREDIENTS

Colloidal Silicon Dioxide, Corn Starch, D&C Red #28, FD&C Blue #1, FD&C Red #40, Gelatin, Anhydrous Lactose, Magnesium Stearate, Silicon Dioxide and Sodium Lauryl Sulfate.

DOSAGE & ADMINISTRATION

Adults and Children 12 years and over: 25 to 50 mg (1 to 2 capsules) every 4 to 6 hours, not to exceed 12 capsules in 24 hours.
•
Children 12 years and under: Consult a Doctor

PURPOSE

Antihistamine

KEEP OUT OF THE REACH OF CHILDREN.

In case of overdose, get medical help or contact a Poison Control Center right away.

ACTIVE INGREDIENT SECTION

Diphenhydramine Hydrochloride 25 mg

Diphenhydramine Hydrochloride 50 mg